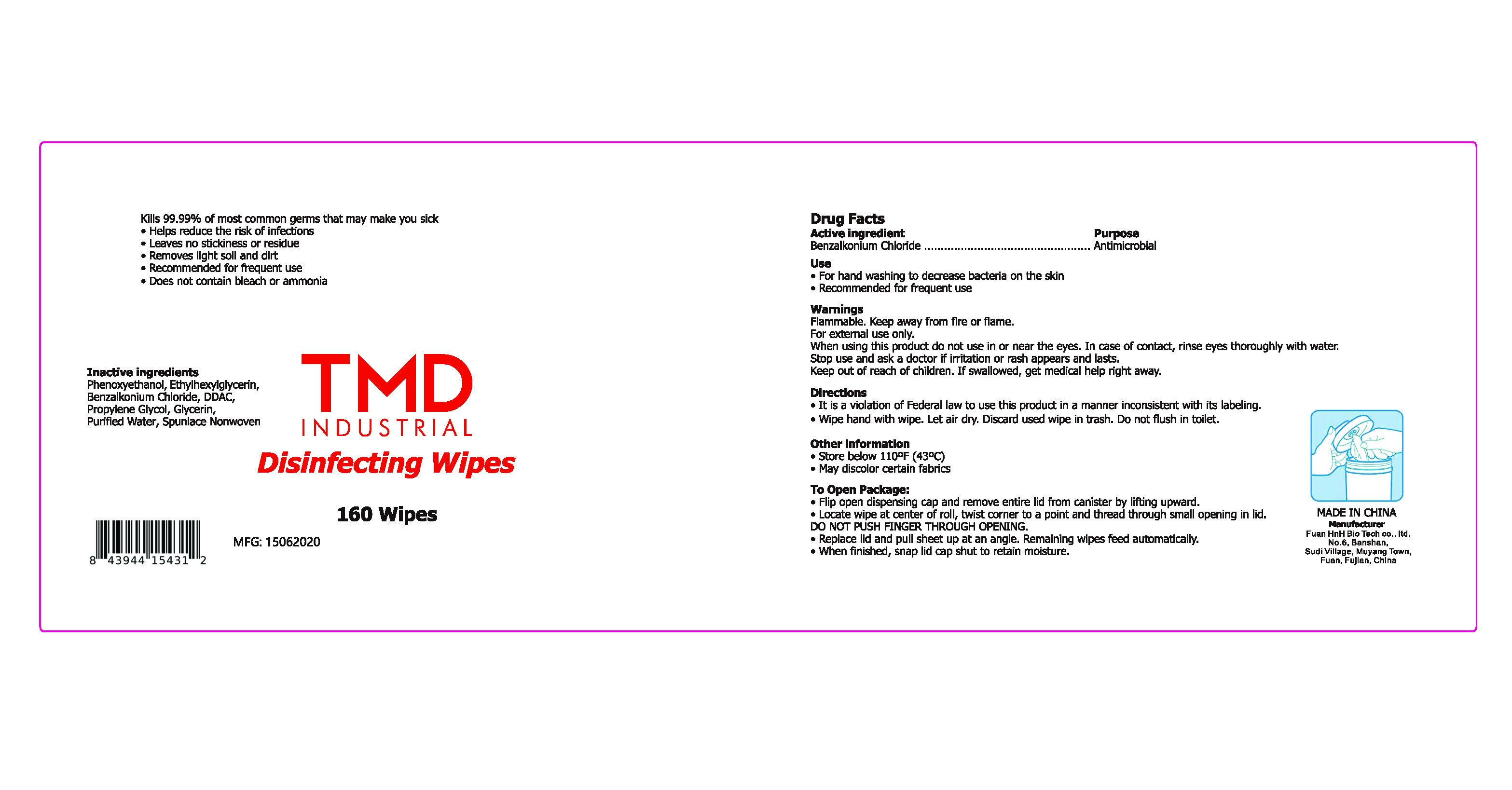 DRUG LABEL: disinfecting wipes
NDC: 79681-201 | Form: CLOTH
Manufacturer: Fuan HnH Bio Tech Co., Ltd.
Category: otc | Type: HUMAN OTC DRUG LABEL
Date: 20200729

ACTIVE INGREDIENTS: DIDECYLDIMONIUM CHLORIDE 0.2 1/100 1; BENZALKONIUM CHLORIDE 0.2 1/100 1
INACTIVE INGREDIENTS: WATER

This is a disinfecting wipes used for hand washing to decrease bacteria on the skin.

The firm does not add other active or inactive ingredients. Different or additional ingredients may impact the quality and potency of the product.

Active Ingredient(s)

Ethanol 75%. Purpose: Antiseptic

Purpose

for hand washing. disinfecting.

Use

for hand washing to decrease bacteria on the skin.

flammable. Keep away from fire or flame. For external use only. When using this product, do not use near the eyes.In case of contact, rinse eyes throughly with water. Stop use and ask a doctor if irritation or rash appears and lasts. Keep out of reach of children. If swallowed, get medial help right away.

For external use only. Flammable. Keep away from heat or flame

Do not use

- in children less than 2 months of age
- on open skin wounds

When using this product keep out of eyes, ears, and mouth. In case of contact with eyes, rinse eyes thoroughly with water.
Stop use and ask a doctor if irritation or rash occurs. These may be signs of a serious condition.
Keep out of reach of children. If swallowed, get medical help or contact a Poison Control Center right away.

Stop use and ask a doctor if irritation or rash occurs. These may be signs of a serious condition.

Keep out of reach of children. If swallowed, get medical help or contact a Poison Control Center right away.

Directions

- Place enough product on hands to cover all surfaces. Rub hands together until dry.
- Supervise children under 6 years of age when using this product to avoid swallowing.

Other information

- Store between 43°(110°F)
- May discolor certain fabrics

Inactive ingredients

Phenoxyethanol, Ethylhexylglycerin, Benzalkonium Chloride, DDAC,

Propylene Glycol, Glycerin, Purified water,Spunlace nonwoven

Package Label - Principal Display Panel

79681-001